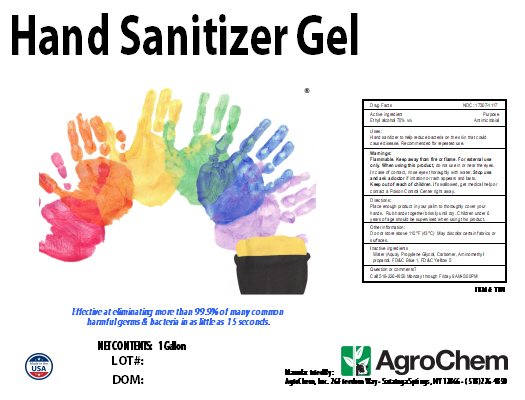 DRUG LABEL: Hand Sanitizer Gel
NDC: 17307-1117 | Form: SOLUTION
Manufacturer: AgroChem Inc
Category: otc | Type: HUMAN OTC DRUG LABEL
Date: 20200925

ACTIVE INGREDIENTS: ALCOHOL 0.7 mL/1 mL
INACTIVE INGREDIENTS: WATER; PROPYLENE GLYCOL; CARBOMER 940; AMINOMETHYLPROPANOL

Hand Sanitizer Gel

Active Ingredient(s)

Ethyl alcohol 70% v/v

Purpose

Antimicrobial

Use

Hand sanitizer to help reduce bacteria on the skin that could cause disease Recommended for repeated use.

Warnings

For external use only. Flammable. Keep away from heat or flame

When using this product do not use in or near the eyes. When using this product keep out of eyes, ears, and mouth. In case of contact with eyes, rinse eyes thoroughly with water.
Stop use and ask a doctor if irritation or rash occurs.

Stop use and ask a doctor if irritation or rash occurs. These may be signs of a serious condition.

Keep out of reach of children. If swallowed, get medical help or contact a Poison Control Center right away.

Directions

Place enough product in your palm to thoroughly cover your hands Rub hands together briskly until dry. Children under 6 years of age should be supervised when using this product.

Other information

Do not store above 110°F (43°C). May discolor certain fabrics or surfaces.

Inactive ingredients

Water (Aqua), Propylene Glycol, Carbomer, Aminomethyl propanol.

DESCRIPTION

Hand Sanitizer Gel

Moisturizing with Aloe

Effective at eliminating more than 99.9% of many common harmful germs & bacteria in as little as 15 seconds.